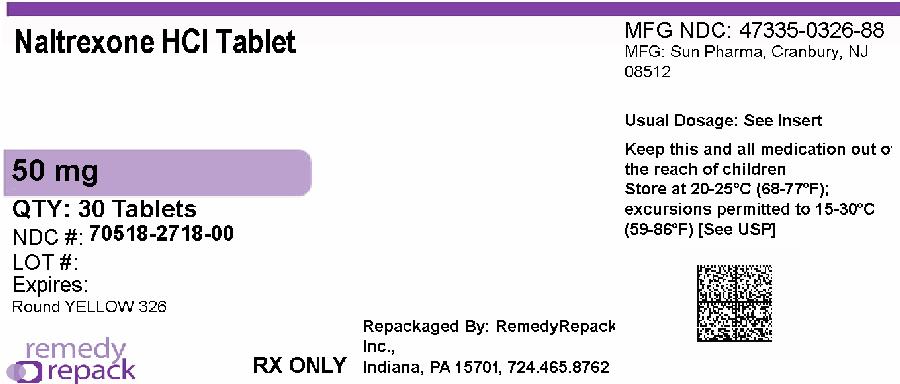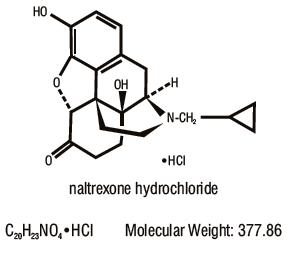 DRUG LABEL: NALTREXONE HYDROCHLORIDE
NDC: 70518-2718 | Form: TABLET, FILM COATED
Manufacturer: REMEDYREPACK INC.
Category: prescription | Type: HUMAN PRESCRIPTION DRUG LABEL
Date: 20260210

ACTIVE INGREDIENTS: NALTREXONE HYDROCHLORIDE 50 mg/1 1
INACTIVE INGREDIENTS: LACTOSE MONOHYDRATE; CELLULOSE, MICROCRYSTALLINE; SILICON DIOXIDE; CROSPOVIDONE; MAGNESIUM STEARATE; HYPROMELLOSE 2910 (6 MPA.S); TITANIUM DIOXIDE; POLYETHYLENE GLYCOL 400; FERRIC OXIDE YELLOW; POLYSORBATE 80; FERRIC OXIDE RED

Naltrexone Hydrochloride Tablets, USP
Opioid Antagonist

DESCRIPTION

Naltrexone hydrochloride, an opioid antagonist, is a synthetic congener of oxymorphone with no opioid agonist properties. Naltrexone hydrochloride differs in structure from oxymorphone in that the methyl group on the nitrogen atom is replaced by a cyclopropylmethyl group. Naltrexone hydrochloride is also related to the potent opioid antagonist, naloxone, or n-allylnoroxymorphone. The chemical name for naltrexone hydrochloride is Morphinan-6-one, 17-(cyclopropylmethyl)-4,5-epoxy-3,14-dihydroxy-, hydrochloride, (5⛙)-. The structural formula is as follows:

Naltrexone hydrochloride is a white, crystalline compound. The hydrochloride salt is soluble in water to the extent of about 100 mg/mL. Naltrexone hydrochloride is available in scored film-coated tablets containing 50 mg of naltrexone hydrochloride, USP. Naltrexone hydrochloride tablets, USP also contain: lactose monohydrate, microcrystalline cellulose, colloidal silicon dioxide, crospovidone, magnesium stearate, hypromellose, titanium dioxide, polyethylene glycol, iron oxide yellow, polysorbate 80 and iron oxide red. test

CLINICAL PHARMACOLOGY

Pharmacodynamic Actions

Naltrexone hydrochloride is a pure opioid antagonist. It markedly attenuates or completely blocks, reversibly, the subjective effects of intravenously administered opioids.

When coadministered with morphine, on a chronic basis, naltrexone hydrochloride blocks the physical dependence to morphine, heroin and other opioids.

Naltrexone hydrochloride has few, if any, intrinsic actions besides its opioid blocking properties. However, it does produce some pupillary constriction, by an unknown mechanism.

The administration of naltrexone hydrochloride is not associated with the development of tolerance or dependence. In subjects physically dependent on opioids, naltrexone hydrochloride will precipitate withdrawal symptomatology.

Clinical studies indicate that 50 mg of naltrexone hydrochloride will block the pharmacologic effects of 25 mg of intravenously administered heroin for periods as long as 24 hours. Other data suggest that doubling the dose of naltrexone hydrochloride provides blockade for 48 hours, and tripling the dose of naltrexone hydrochloride provides blockade for about 72 hours.

Naltrexone hydrochloride blocks the effects of opioids by competitive binding (i.e., analogous to competitive inhibition of enzymes) at opioid receptors. This makes the blockade produced potentially surmountable, but overcoming full naltrexone blockade by administration of very high doses of opiates has resulted in excessive symptoms of histamine release in experimental subjects.

The mechanism of action of naltrexone hydrochloride in alcoholism is not understood; however, involvement of the endogenous opioid system is suggested by preclinical data. Naltrexone hydrochloride, an opioid receptor antagonist, competitively binds to such receptors and may block the effects of endogenous opioids. Opioid antagonists have been shown to reduce alcohol consumption by animals, and naltrexone hydrochloride has been shown to reduce alcohol consumption in clinical studies.

Naltrexone hydrochloride is not aversive therapy and does not cause a disulfiram-like reaction either as a result of opiate use or ethanol ingestion.

Pharmacokinetics

Naltrexone hydrochloride is a pure opioid receptor antagonist. Although well absorbed orally, naltrexone is subject to significant first pass metabolism with oral bioavailability estimates ranging from 5 to 40%. The activity of naltrexone is believed to be due to both parent and the 6-ß-naltrexol metabolite. Both parent drug and metabolites are excreted primarily by the kidney (53% to 79% of the dose), however, urinary excretion of unchanged naltrexone accounts for less than 2% of an oral dose and fecal excretion is a minor elimination pathway. The mean elimination half-life (T-1/2) values for naltrexone and 6-ß-naltrexol are 4 hours and 13 hours, respectively. Naltrexone and 6-ß-naltrexol are dose proportional in terms of AUC and Cmaxover the range of 50 to 200 mg and do not accumulate after 100 mg daily doses.

Absorption:

Following oral administration, naltrexone undergoes rapid and nearly complete absorption with approximately 96% of the dose absorbed from the gastrointestinal tract. Peak plasma levels of both naltrexone and 6-ß-naltrexol occur within one hour of dosing.

Distribution:

The volume of distribution for naltrexone following intravenous administration is estimated to be 1350 liters. In vitro tests with human plasma show naltrexone to be 21% bound to plasma proteins over the therapeutic dose range.

Metabolism:

The systemic clearance (after intravenous administration) of naltrexone is ~ 3.5 L/min, which exceeds liver blood flow (~ 1.2 L/min). This suggests both that naltrexone is a highly extracted drug (>98% metabolized) and that extrahepatic sites of drug metabolism exist. The major metabolite of naltrexone is 6-ß-naltrexol. Two other minor metabolites are 2-hydroxy-3-methoxy-6-ß-naltrexol and 2-hydroxy-3-methyl-naltrexone. Naltrexone and its metabolites are also conjugated to form additional metabolic products.

Elimination:

The renal clearance for naltrexone ranges from 30 to 127 mL/min and suggests that renal elimination is primarily by glomerular filtration. In comparison the renal clearance for 6-ß-naltrexol ranges from 230 to 369 mL/min, suggesting an additional renal tubular secretory mechanism. The urinary excretion of unchanged naltrexone accounts for less than 2% of an oral dose; urinary excretion of unchanged and conjugated 6-ß-naltrexol accounts for 43% of an oral dose. The pharmacokinetic profile of naltrexone suggests that naltrexone and its metabolites may undergo enterohepatic recycling.

Hepatic and Renal Impairment:

Naltrexone appears to have extra-hepatic sites of drug metabolism and its major metabolite undergoes active tubular secretion (see Metabolismabove). Adequate studies of naltrexone in patients with severe hepatic or renal impairment have not been conducted (see PRECAUTIONS: Special Risk Patients).

Clinical Trials

Alcoholism:

The efficacy of naltrexone hydrochloride as an aid to the treatment of alcoholism was tested in placebo-controlled, outpatient, double blind trials. These studies used a dose of naltrexone hydrochloride 50 mg once daily for 12 weeks as an adjunct to social and psychotherapeutic methods when given under conditions that enhanced patient compliance. Patients with psychosis, dementia, and secondary psychiatric diagnoses were excluded from these studies.
In one of these studies, 104 alcohol-dependent patients were randomized to receive either naltrexone hydrochloride 50 mg once daily or placebo. In this study, naltrexone

hydrochloride proved superior to placebo in measures of drinking including abstention rates (51% vs. 23%), number of drinking days, and relapse (31% vs. 60%). In a second study with 82 alcohol-dependent patients, the group of patients receiving naltrexone hydrochloride were shown to have lower relapse rates (21% vs. 41%), less alcohol craving, and fewer drinking days compared with patients who received placebo, but these results depended on the specific analysis used.

The clinical use of naltrexone hydrochloride as adjunctive pharmacotherapy for the treatment of alcoholism was also evaluated in a multicenter safety study. This study of 865 individuals with alcoholism included patients with comorbid psychiatric conditions, concomitant medications, polysubstance abuse and HIV disease. Results of this study demonstrated that the side effect profile of naltrexone hydrochloride appears to be similar in both alcoholic and opioid dependent populations, and that serious side effects are uncommon.

In the clinical studies, treatment with naltrexone hydrochloride supported abstinence, prevented relapse and decreased alcohol consumption. In the uncontrolled study, the patterns of abstinence and relapse were similar to those observed in the controlled studies. Naltrexone hydrochloride was not uniformly helpful to all patients, and the expected effect of the drug is a modest improvement in the outcome of conventional treatment.

Treatment of Opioid Addiction:

Naltrexone hydrochloride has been shown to produce complete blockade of the euphoric effects of opioids in both volunteer and addict populations. When administered by means that enforce compliance, it will produce an effective opioid blockade, but has not been shown to affect the use of cocaine or other non-opioid drugs of abuse.

There are no data that demonstrate an unequivocally beneficial effect of naltrexone hydrochloride on rates of recidivism among detoxified, formerly opioid-dependent individuals who self-administer the drug. The failure of the drug in this setting appears to be due to poor medication compliance.

The drug is reported to be of greatest use in good prognosis opioid addicts who take the drug as part of a comprehensive occupational rehabilitative program, behavioral contract, or other compliance-enhancing protocol. Naltrexone hydrochloride, unlike methadone or LAAM (levo-alpha-acetyl-methadol), does not reinforce medication compliance and is expected to have a therapeutic effect only when given under external conditions that support continued use of the medication.

INDICATIONS AND USAGE

Naltrexone hydrochloride tablets are indicated in the treatment of alcohol dependence and for the blockade of the effects of exogenously administered opioids.

Naltrexone hydrochloride has not been shown to provide any therapeutic benefit except as part of an appropriate plan of management for the addictions.

CONTRAINDICATIONS

Naltrexone hydrochloride is contraindicated in:

1. Patients receiving opioid analgesics.
2. Patients currently dependent on opioids, including those currently maintained on opiate agonists [e.g., methadone) or partial agonists (e.g., buprenorphine).
3. Patients in acute opioid withdrawal (see WARNINGS).
4. Any individual who has failed the naloxone challenge test or who has a positive urine screen for opioids.
5. Any individual with a history of sensitivity to naltrexone hydrochloride or any other components of this product. It is not known if there is any cross-sensitivity with naloxone or the phenanthrene containing opioids.

WARNINGS

Vulnerability to Opioid Overdose

After opioid detoxification, patients are likely to have reduced tolerance to opioids. As the blockade of exogenous opioids provided by naltrexone hydrochloride wanes and eventually dissipates completely, patients who have been treated with naltrexone hydrochloride may respond to lower doses of opioids than previously used, just as they would shortly after completing detoxification.

This could result in potentially life-threatening opioid intoxication (respiratory compromise or arrest, circulatory collapse, etc.) if the patient uses previously tolerated doses of opioids. Cases of opioid overdose with fatal outcomes have been reported in patients after discontinuing treatment.

Patients should be alerted that they may be more sensitive to opioids, even at lower doses, after naltrexone hydrochloride treatment is discontinued. It is important that patients inform family members, and the people closest to the patient of this increased sensitivity to opioids and the risk of overdose (see PRECAUTIONS, Information for Patients).

There is also the possibility that a patient who is treated with naltrexone hydrochloride could overcome the opioid blockade effect of naltrexone hydrochloride. Although naltrexone hydrochloride is a potent antagonist, the blockade produced by naltrexone hydrochloride is surmountable. The plasma concentration of exogenous opioids attained immediately following their acute administration may be sufficient to overcome the competitive receptor blockade. This poses a potential risk to individuals who attempt, on their own, to overcome the blockade by administering large amounts of exogenous opioids. Any attempt by a patient to overcome the antagonism by taking opioids is especially dangerous and may lead to life-threatening opioid intoxication or fatal overdose. Patients should be told of the serious consequences of trying to overcome the opioid blockade (see PRECAUTIONS, Information for Patients).

Precipitated Opioid Withdrawal

The symptoms of spontaneous opioid withdrawal (which are associated with the discontinuation of opioid in a dependent individual) are uncomfortable, but they are not generally believed to be severe or necessitate hospitalization. However, when withdrawal is precipitated abruptly by the administration of an opioid antagonist to an opioid-dependent patient, the resulting withdrawal syndrome can be severe enough to require hospitalization. Symptoms of withdrawal have usually appeared within five minutes of ingestion of naltrexone hydrochloride and have lasted for up to 48 hours. Mental status changes including confusion, somnolence and visual hallucinations have occurred. Significant fluid losses from vomiting and diarrhea have required intravenous fluid administration. Review of postmarketing cases of precipitated opioid withdrawal in association with naltrexone treatment has identified cases with symptoms of withdrawal severe enough to require hospital admission, and in some cases, management in the intensive care unit.

To prevent occurrence of precipitated withdrawal in patients dependent on opioids, or exacerbation of a preexisting subclinical withdrawal syndrome, opioid-dependent patients, including those being treated for alcohol dependence, should be opioid-free (including tramadol) before starting naltrexone hydrochloride treatment. An opioid-free interval of a minimum of 7 to 10 days is recommended for patients previously dependent on short-acting opioids. Patients transitioning from buprenorphine or methadone may be vulnerable to precipitation of withdrawal symptoms for as long as two weeks.

If a more rapid transition from agonist to antagonist therapy is deemed necessary and appropriate by the healthcare provider, monitor the patient closely in an appropriate medical setting where precipitated withdrawal can be managed.

In every case, healthcare providers should always be prepared to manage withdrawal symptomatically with non-opioid medications because there is no completely reliable method for determining whether a patient has had an adequate opioid-free period. A naloxone challenge test may be helpful; however, a few case reports have indicated that patients may experience precipitated withdrawal despite having a negative urine toxicology screen or tolerating a naloxone challenge test (usually in the setting of transitioning from buprenorphine treatment). Patients should be made aware of the risks associated with precipitated withdrawal and encouraged to give an accurate account of last opioid use. Patients treated for alcohol dependence with naltrexone hydrochloride should also be assessed for underlying opioid dependence and for any recent use of opioids prior to initiation of treatment with naltrexone hydrochloride. Precipitated opioid withdrawal has been observed in alcohol-dependent patients in circumstances where the prescriber had been unaware of the additional use of opioids or co-dependence on opioids.

Hepatotoxicity

Cases of hepatitis and clinically significant liver dysfunction were observed in association with naltrexone hydrochloride exposure during the clinical development program and in the postmarketing period. Transient, asymptomatic hepatic transaminase elevations were also observed in the clinical trials and postmarketing period. When patients presented with elevated transaminases, there were often other potential causative or contributory etiologies identified, including preexisting alcoholic liver disease, hepatitis B and/or C infection, and concomitant usage of other potentially hepatotoxic drugs. Although clinically significant liver dysfunction is not typically recognized as a manifestation of opioid withdrawal, opioid withdrawal that is precipitated abruptly may lead to systemic sequelae, including acute liver injury. Patients should be warned of the risk of hepatic injury and advised to seek medical attention if they experience symptoms of acute hepatitis. Use of naltrexone hydrochloride should be discontinued in the event of symptoms and/or signs of acute hepatitis. Depression and Suicidality Depression, suicide, attempted suicide and suicidal ideation have been reported in the postmarketing experience with naltrexone hydrochloride used in the treatment of opioid dependence. No causal relationship has been demonstrated. In the literature, endogenous opioids have been theorized to contribute to a variety of conditions. Alcohol-and opioid-dependent patients, including those taking naltrexone hydrochloride, should be monitored for the development of depression or suicidal thinking. Families and caregivers of patients being treated with naltrexone hydrochloride should be alerted to the need to monitor patients for the emergence of symptoms of depression or suicidality, and to report such symptoms to the patient’s healthcare provider.

Ultra Rapid Opioid Withdrawal:

Safe use of naltrexone hydrochloride in ultra rapid opiate detoxification programs has not been established (see ADVERSE REACTIONS).

PRECAUTIONS

General

When Reversal of Naltrexone Hydrochloride Blockade is Required for Pain Management:In an emergency situation in patients receiving fully blocking doses of naltrexone hydrochloride, a suggested plan of management is regional analgesia, conscious sedation with a benzodiazepine, use of non-opioid analgesics or general anesthesia.

In a situation requiring opioid analgesia, the amount of opioid required may be greater than usual, and the resulting respiratory depression may be deeper and more prolonged.

A rapidly acting opioid analgesic which minimizes the duration of respiratory depression is preferred. The amount of analgesic administered should be titrated to the needs of the patient. Non-receptor mediated actions may occur and should be expected (e.g., facial swelling, itching, generalized erythema, or bronchoconstriction) presumably due to histamine release.

Irrespective of the drug chosen to reverse naltrexone hydrochloride blockade, the patient should be monitored closely by appropriately trained personnel in a setting equipped and staffed for cardiopulmonary resuscitation.

Special Risk Patients

Renal Impairment:Naltrexone hydrochloride and its primary metabolite are excreted primarily in the urine, and caution is recommended in administering the drug to patients with renal impairment.

Hepatic Impairment:An increase in naltrexone AUC of approximately 5-and 10-fold in patients with compensated and decompensated liver cirrhosis, respectively, compared with subjects with normal liver function has been reported. These data also suggest that alterations in naltrexone bioavailability are related to liver disease severity.

Information for Patients

It is recommended that the prescribing physician relate the following information to patients being treated with naltrexone hydrochloride:

You have been prescribed naltrexone hydrochloride tablets as part of the comprehensive treatment for your alcoholism or drug dependence. You should carry identification to alert medical personnel to the fact that you are taking naltrexone hydrochloride. A naltrexone hydrochloride medication card may be obtained from your physician and can be used for this purpose. Carrying the identification card should help to ensure that you can obtain adequate treatment in an emergency. If you require medical treatment, be sure to tell the treating physician that you are receiving naltrexone hydrochloride therapy. You should take naltrexone hydrochloride as directed by your physician.

- Advise patients that if they previously used opioids, they may be more sensitive to lower doses of opioids and at risk of accidental overdose should they use opioids after naltrexone hydrochloride treatment is discontinued or temporarily interrupted. It is important that patients inform family members and the people closest to the patient of this increased sensitivity to opioids and the risk of overdose.
- Advise patients that because naltrexone hydrochloride can block the effects of opioids, patients will not perceive any effect if they attempt to self-administer heroin or any other opioid drug in small doses while on naltrexone hydrochloride tablets. Further, emphasize that administration of large doses of heroin or any other opioid to try to bypass the blockade and get high while on naltrexone hydrochloride may lead to serious injury, coma, or death.
- Patients on naltrexone hydrochloride tablets may not experience the expected effects from opioid-containing analgesic, antidiarrheal, or antitussive medications.
- Patients should be off all opioids, including opioid-containing medicines, for a minimum of 7 to 10 days before starting naltrexone hydrochloride tablets in order to avoid precipitation of opioid withdrawal. Patients transitioning from buprenorphine or methadone may be vulnerable to precipitation of withdrawal symptoms for as long as two weeks. Ensure that patients understand that withdrawal precipitated by administration of an opioid antagonist may be severe enough to require hospitalization if they have not been opioid-free for an adequate period of time, and is different from the experience of spontaneous withdrawal that occurs with discontinuation of opioid in a dependent individual. Advise patients that they should not take naltrexone hydrochloride tablets if they have any symptoms of opioid withdrawal. Advise all patients, including those with alcohol dependence, that it is imperative to notify healthcare providers of any recent use of opioids or any history of opioid dependence before starting naltrexone hydrochloride to avoid precipitation of opioid withdrawal.
- Advise patients that naltrexone hydrochloride tablets may cause liver injury. Patients should immediately notify their physician if they develop symptoms and/or signs of liver disease.
- Advise patients that they may experience depression while taking naltrexone hydrochloride tablets. It is important that patients inform family members and the people closest to the patient that they are taking naltrexone hydrochloride and that they should call a doctor right away should they become depressed or experience symptoms of depression.
- Advise patients that naltrexone hydrochloride has been shown to be effective only when used as part of a treatment program that includes counseling and support.
- Advise patients that dizziness may occur with naltrexone hydrochloride treatment, and they should avoid driving or operating heavy machinery until they have determined how naltrexone hydrochloride affects them.
- Advise patients to notify their physician if they:
  - become pregnant or intend to become pregnant during treatment with naltrexone hydrochloride.
  - are breast-feeding.
  - experience other unusual or significant side effects while on naltrexone hydrochloride therapy.

Repackaged By / Distributed By: RemedyRepack Inc.

625 Kolter Drive, Indiana, PA 15701

(724) 465-8762

Laboratory Tests

Naltrexone hydrochloride does not interfere with thin-layer, gas-liquid, and high pressure liquid chromatographic methods which may be used for the separation and detection of morphine, methadone or quinine in the urine. Naltrexone hydrochloride may or may not interfere with enzymatic methods for the detection of opioids depending on the specificity of the test. Please consult the test manufacturer for specific details.

Drug Interactions

Studies to evaluate possible interactions between naltrexone hydrochloride and drugs other than opiates have not been performed. Consequently, caution is advised if the concomitant administration of naltrexone hydrochloride and other drugs is required.

The safety and efficacy of concomitant use of naltrexone hydrochloride and disulfiram is unknown, and the concomitant use of two potentially hepatotoxic medications is not ordinarily recommended unless the probable benefits outweigh the known risks.

Lethargy and somnolence have been reported following doses of naltrexone hydrochloride and thioridazine.

Patients taking naltrexone hydrochloride may not benefit from opioid containing medicines, such as cough and cold preparations, antidiarrheal preparations, and opioid analgesics. In an emergency situation when opioid analgesia must be administered to a patient receiving naltrexone hydrochloride, the amount of opioid required may be greater than usual, and the resulting respiratory depression may be deeper and more prolonged (see PRECAUTIONS).

Carcinogenesis, Mutagenesis and Impairment of Fertility

The following statements are based on the results of experiments in mice and rats. The potential carcinogenic, mutagenic and fertility effects of the metabolite 6-β-naltrexol are unknown.

In a two-year carcinogenicity study in rats, there were small increases in the numbers of testicular mesotheliomas in males and tumors of vascular origin in males and females. The incidence of mesothelioma in males given naltrexone at a dietary dose of 100 mg/kg/day (600 mg/m^2/day; 16 times the recommended therapeutic dose, based on body surface area) was 6%, compared with a maximum historical incidence of 4%. The incidence of vascular tumors in males and females given dietary doses of 100 mg/kg/day (600 mg/m^2/day) was 4% but only the incidence in females was increased compared with a maximum historical control incidence of 2%. There was no evidence of carcinogenicity in a two-year dietary study with naltrexone in male and female mice.

There was limited evidence of a weak genotoxic effect of naltrexone in one gene mutation assay in a mammalian cell line, in the Drosophilarecessive lethal assay, and in non-specific DNA repair tests with E. coli. However, no evidence of genotoxic potential was observed in a range of other in vitrotests, including assays for gene mutation in bacteria, yeast, or in a second mammalian cell line, a chromosomal aberration assay, and an assay for DNA damage in human cells. Naltrexone did not exhibit clastogenicity in an in vivomouse micronucleus assay.

Naltrexone (100 mg/kg/day [600 mg/m^2/day] PO; 16 times the recommended therapeutic dose, based on body surface area) caused a significant increase in pseudopregnancy in the rat. A decrease in the pregnancy rate of mated female rats also occurred. There was no effect on male fertility at this dose level. The relevance of these observations to human fertility is not known.

Pregnancy

Teratogenic Effects: Pregnancy Category C:Naltrexone has been shown to increase the incidence of early fetal loss when given to rats at doses ≥ 30 mg/kg/day (180 mg/m^2/day; 5 times the recommended therapeutic dose, based on body surface area) and to rabbits at oral doses ≥ 60 mg/kg/day (720 mg/m^2/day; 18 times the recommended therapeutic dose, based on body surface area). There was no evidence of teratogenicity when naltrexone was administered orally to rats and rabbits during the period of major organogenesis at doses up to 200 mg/kg/day (32 and 65 times the recommended therapeutic dose, respectively, based on body surface area).

Rats do not form appreciable quantities of the major human metabolites, 6-β-naltrexol; therefore, the potential reproductive toxicity of the metabolite in rats is not known.

There are no adequate and well-controlled studies in pregnant women. Naltrexone hydrochloride should be used during pregnancy only if the potential benefit justifies the potential risk to the fetus.

Labor and Delivery

Whether or not naltrexone hydrochloride affects the duration of labor and delivery is unknown.

Nursing Mothers

In animal studies, naltrexone and 6-β-naltrexol were excreted in the milk of lactating rats dosed orally with naltrexone. Whether or not naltrexone hydrochloride is excreted in human milk is unknown. Because many drugs are excreted in human milk, caution should be exercised when naltrexone hydrochloride is administered to a nursing woman.

Pediatric Use

The safe use of naltrexone hydrochloride in pediatric patients younger than 18 years old has not been established.

ADVERSE REACTIONS

During two randomized, double-blind, placebo-controlled 12 week trials to evaluate the efficacy of naltrexone hydrochloride as an adjunctive treatment of alcohol dependence, most patients tolerated naltrexone hydrochloride well. In these studies, a total of 93 patients received naltrexone hydrochloride at a dose of 50 mg once daily. Five of these patients discontinued naltrexone hydrochloride because of nausea. No serious adverse events were reported during these two trials.

While extensive clinical studies evaluating the use of naltrexone hydrochloride in detoxified, formerly opioid-dependent individuals failed to identify any single, serious untoward risk of naltrexone hydrochloride use, placebo-controlled studies employing up to fivefold higher doses of naltrexone hydrochloride (up to 300 mg per day) than that recommended for use in opiate receptor blockade have shown that naltrexone hydrochloride causes hepatocellular injury in a substantial proportion of patients exposed at higher doses (see WARNINGSand PRECAUTIONS: Laboratory Tests).

Aside from this finding, and the risk of precipitated opioid withdrawal, available evidence does not incriminate naltrexone hydrochloride, used at any dose, as a cause of any other serious adverse reaction for the patient who is “opioid-free.” It is critical to recognize that naltrexone hydrochloride can precipitate or exacerbate abstinence signs and symptoms in any individual who is not completely free of exogenous opioids.

Patients with addictive disorders, especially opioid addiction, are at risk for multiple numerous adverse events and abnormal laboratory findings, including liver function abnormalities. Data from both controlled and observational studies suggest that these abnormalities, other than the dose-related hepatotoxicity described above, are not related to the use of naltrexone hydrochloride.

Among opioid-free individuals, naltrexone hydrochloride administration at the recommended dose has not been associated with a predictable profile of serious adverse or untoward events. However, as mentioned above, among individuals using opioids, naltrexone hydrochloride may cause serious withdrawal reactions (see CONTRAINDICATIONS, WARNINGS, DOSAGE AND ADMINISTRATION).

Reported Adverse Events

Naltrexone hydrochloride has not been shown to cause significant increases in complaints in placebo-controlled trials in patients known to be free of opioids for more than 7 to 10 days. Studies in alcoholic populations and in volunteers in clinical pharmacology studies have suggested that a small fraction of patients may experience an opioid withdrawal-like symptom complex consisting of tearfulness, mild nausea, abdominal cramps, restlessness, bone or joint pain, myalgia, and nasal symptoms. This may represent the unmasking of occult opioid use, or it may represent symptoms attributable to naltrexone. A number of alternative dosing patterns have been recommended to try to reduce the frequency of these complaints.

Alcoholism

In an open label safety study with approximately 570 individuals with alcoholism receiving naltrexone hydrochloride, the following new-onset adverse reactions occurred in 2% or more of the patients: nausea (10%), headache (7%), dizziness (4%), nervousness (4%), fatigue (4%), insomnia (3%), vomiting (3%), anxiety (2%) and somnolence (2%).

Depression, suicidal ideation, and suicidal attempts have been reported in all groups when comparing naltrexone, placebo, or controls undergoing treatment for alcoholism.

 | RATE RANGES OF NEW ONSET EVENTS
 | Naltrexone | Placebo
Depression | 0 to 15% | 0 to 17%
Suicide Attempt/Ideation | 0 to 1% | 0 to 3%

Although no causal relationship with naltrexone hydrochloride is suspected, physicians should be aware that treatment with naltrexone hydrochloride does not reduce the risk of suicide in these patients (see PRECAUTIONS).

Opioid Addiction

The following adverse reactions have been reported both at baseline and during the naltrexone hydrochloride clinical trials in opioid addiction at an incidence rate of more than 10%:
Difficulty sleeping, anxiety, nervousness, abdominal pain/cramps, nausea and/or vomiting, low energy, joint and muscle pain, and headache.
The incidence was less than 10% for:
Loss of appetite, diarrhea, constipation, increased thirst, increased energy, feeling down, irritability, dizziness, skin rash, delayed ejaculation, decreased potency, and chills.
The following events occurred in less than 1% of subjects:
Respiratory:Nasal congestion, itching, rhinorrhea, sneezing, sore throat, excess mucus or phlegm, sinus trouble, heavy breathing, hoarseness, cough, shortness of breath.
Cardiovascular: Nose bleeds, phlebitis, edema, increased blood pressure, non-specific ECG changes, palpitations, tachycardia.
Gastrointestinal: Excessive gas, hemorrhoids, diarrhea, ulcer.
Musculoskeletal:Painful shoulders, legs or knees; tremors, twitching.
Genitourinary: Increased frequency of, or discomfort during, urination; increased or decreased sexual interest.
Dermatologic: Oily skin, pruritus, acne, athlete’s foot, cold sores, alopecia.
Psychiatric: Depression, paranoia, fatigue, restlessness, confusion, disorientation, hallucinations, nightmares, bad dreams.
Special senses: Eyes-blurred, burning, light sensitive, swollen, aching, strained; ears-“clogged”, aching, tinnitus.
General: Increased appetite, weight loss, weight gain, yawning, somnolence, fever, dry mouth, head “pounding”, inguinal pain, swollen glands, “side” pains, cold feet, “hot spells.”
Postmarketing Experience: Data collected from postmarketing use of naltrexone hydrochloride show that most events usually occur early in the course of drug therapy and are transient. It is not always possible to distinguish these occurrences from those signs and symptoms that may result from a withdrawal syndrome. Events that have been reported include anorexia, asthenia, chest pain, fatigue, headache, hot flushes, malaise, changes in blood pressure, agitation, dizziness, hyperkinesia, nausea, vomiting, tremor, abdominal pain, diarrhea, palpitations, myalgia, anxiety, confusion, euphoria, hallucinations, insomnia, nervousness, somnolence, abnormal thinking, dyspnea, rash, increased sweating, vision abnormalities, and idiopathic thrombocytopenic purpura.
In some individuals the use of opioid antagonists has been associated with a change in baseline levels of some hypothalamic, pituitary, adrenal, or gonadal hormones. The clinical significance of such changes is not fully understood.
Adverse events, including withdrawal symptoms and death, have been reported with the use of naltrexone hydrochloride in ultra rapid opiate detoxification programs. The cause of death in these cases is not known (see WARNINGS).
Laboratory Tests:
In a placebo controlled study in which naltrexone hydrochloride was administered to obese subjects at a dose approximately five-fold that recommended for the blockade of opiate receptors (300 mg per day), 19% (5/26) of naltrexone hydrochloride recipients and 0% (0/24) of placebo-treated patients developed elevations of serum transaminases (i.e., peak ALT values ranging from 121 to 532; or 3 to 19 times their baseline values) after three to eight weeks of treatment. The patients involved were generally clinically asymptomatic, and the transaminase levels of all patients on whom follow-up was obtained returned to (or toward) baseline values in a matter of weeks.
Transaminase elevations were also observed in other placebo controlled studies in which exposure to naltrexone hydrochloride at doses above the amount recommended for the treatment of alcoholism or opioid blockade consistently produced more numerous and more significant elevations of serum transaminases than did placebo. Transaminase elevations occurred in 3 of 9 patients with Alzheimer's Disease who received naltrexone hydrochloride (at doses up to 300 mg/day) for 5 to 8 weeks in an open clinical trial.

DRUG ABUSE AND DEPENDENCE

Naltrexone hydrochloride is a pure opioid antagonist. It does not lead to physical or psychological dependence. Tolerance to the opioid antagonist effect is not known to occur.

OVERDOSAGE

There is limited clinical experience with naltrexone hydrochloride overdosage in humans. In one study, subjects who received 800 mg daily naltrexone hydrochloride for up to one week showed no evidence of toxicity.

In the mouse, rat and guinea pig, the oral LD50s were 1,100 to 1,550 mg/kg; 1,450 mg/kg; and 1,490 mg/kg; respectively. High doses of naltrexone hydrochloride (generally ≥1,000 mg/kg) produced salivation, depression/reduced activity, tremors, and convulsions. Mortalities in animals due to high-dose naltrexone hydrochloride administration usually were due to clonic-tonic convulsions and/or respiratory failure.
Treatment of Overdosage
In view of the lack of actual experience in the treatment of naltrexone hydrochloride overdose, patients should be treated symptomatically in a closely supervised environment. Physicians should contact a poison control center for the most up-to-date information.

DOSAGE AND ADMINISTRATION

To reduce the risk of precipitated withdrawal in patients dependent on opioids, or exacerbation of a preexisting subclinical withdrawal syndrome, opioid-dependent patients, including those being treated for alcohol dependence, should be opioid-free (including tramadol) before starting naltrexone hydrochloride treatment. An opioid-free interval of a minimum of 7 to 10 days is recommended for patients previously dependent on short-acting opioids.

Switching from Buprenorphine, Buprenorphine/Naloxone, or Methadone

There are no systematically collected data that specifically address the switch from buprenorphine or methadone to naltrexone hydrochloride; however, review of postmarketing case reports have indicated that some patients may experience severe manifestations of precipitated withdrawal when being switched from opioid agonist therapy to opioid antagonist therapy (see WARNINGS). Patients transitioning from buprenorphine or methadone may be vulnerable to precipitation of withdrawal symptoms for as long as 2 weeks. Healthcare providers should be prepared to manage withdrawal symptomatically with non-opioid medications.

Treatment of Alcoholism

A dose of 50 mg once daily is recommended for most patients. The placebo-controlled studies that demonstrated the efficacy of naltrexone hydrochloride as an adjunctive treatment of alcoholism used a dose regimen of naltrexone hydrochloride 50 mg once daily for up to 12 weeks. Other dose regimens or durations of therapy were not evaluated in these trials.

Naltrexone hydrochloride should be considered as only one of many factors determining the success of treatment of alcoholism. Factors associated with a good outcome in the clinical trials with naltrexone hydrochloride were the type, intensity, and duration of treatment; appropriate management of comorbid conditions; use of community-based support groups; and good medication compliance. To achieve the best possible treatment outcome, appropriate compliance-enhancing techniques should be implemented for all components of the treatment program, especially medication compliance.

Treatment of Opioid Dependence

Treatment should be initiated with an initial dose of 25 mg of naltrexone hydrochloride. If no withdrawal signs occur, the patient may be started on 50 mg a day thereafter.
A dose of 50 mg once a day will produce adequate clinical blockade of the actions of parenterally administered opioids. As with many non-agonist treatments for addiction, naltrexone hydrochloride is of proven value only when given as part of a comprehensive plan of management that includes some measure to ensure the patient takes the medication.

Naloxone Challenge Test

Clinicians are reminded that there is no completely reliable method for determining whether a patient has had an adequate opioid-free period. A naloxone challenge test may be helpful if there is any question of occult opioid dependence. If signs of opioid withdrawal are still observed following naloxone challenge, treatment with naltrexone hydrochlorideshould not be attempted. The naloxone challenge can be repeated in 24 hours. The naloxone challenge test should not be performed in a patient showing clinical signs or symptoms of opioid withdrawal, or in a patient whose urine contains opioids. The naloxone challenge test may be administered by either the intravenous or subcutaneous routes.
Intravenous:

Inject 0.2 mg naloxone.

Observe for 30 seconds for signs or symptoms of withdrawal.

If no evidence of withdrawal, inject 0.6 mg of naloxone.

Observe for an additional 20 minutes.
Subcutaneous:

Administer 0.8 mg naloxone.

Observe for 20 minutes for signs or symptoms of withdrawal.

Note: Individual patients, especially those with opioid dependence, may respond to lower doses of naloxone. In some cases, 0.1 mg IV naloxone has produced a diagnostic response.

Interpretation of the Challenge

Monitor vital signs and observe the patient for signs and symptoms of opioid withdrawal. These may include, but are not limited to: nausea, vomiting, dysphoria, yawning, sweating, tearing, rhinorrhea, stuffy nose, craving for opioids, poor appetite, abdominal cramps, sense of fear, skin erythema, disrupted sleep patterns, fidgeting, uneasiness, poor ability to focus, mental lapses, muscle aches or cramps, pupillary dilation, piloerection, fever, changes in blood pressure, pulse or temperature, anxiety, depression, irritability, backache, bone or joint pains, tremors, sensations of skin crawling or fasciculations. If signs or symptoms of withdrawal appear, the test is positive and no additional naloxone should be administered.

Warning: If the test is positive, do NOT initiatenaltrexone hydrochloride therapy.Repeat the challenge in 24 hours. If the test is negative, naltrexone hydrochloride therapy may be started if no other contraindications are present. If there is any doubt about the result of the test, hold naltrexone hydrochloride and repeat the challenge in 24 hours.

Alternative Dosing Schedules

A flexible approach to a dosing regimen may need to be employed in cases of supervised administration. Thus, patients may receive 50 mg of naltrexone hydrochloride every weekday with a 100 mg dose on Saturday, 100 mg every other day, or 150 mg every third day. The degree of blockade produced by naltrexone hydrochloride may be reduced by these extended dosing intervals.

There may be a higher risk of hepatocellular injury with single doses above 50 mg, and use of higher doses and extended dosing intervals should balance the possible risks against the probable benefits (see WARNINGS).

Patient Compliance

Naltrexone hydrochloride should be considered as only one of many factors determining the success of treatment. To achieve the best possible treatment outcome, appropriate compliance-enhancing techniques should be implemented for all components of the treatment program, including medication compliance.

HOW SUPPLIED

Naltrexone Hydrochloride Tablets, USP are available as follows: 50 mg: Yellow, round, biconvex, film-coated tablets debossed with “326” on one side and scored on other side.

NDC: 70518-2718-00

NDC: 70518-2718-01

PACKAGING: 30 in 1 BLISTER PACK

PACKAGING: 28 in 1 BLISTER PACK

Store at 20° to 25°C (68° to 77°F); excursions permitted between 15° and 30°C (59° and 86°F) [see USP Controlled Room Temperature].

Dispense in a tight container.

Repackaged and Distributed By:

Remedy Repack, Inc.

625 Kolter Dr. Suite #4 Indiana, PA 1-724-465-8762

Repackaged and Distributed By:

Remedy Repack, Inc.

625 Kolter Dr. Suite #4 Indiana, PA 1-724-465-8762

PACKAGE LABEL

DRUG: NALTREXONE HYDROCHLORIDE

GENERIC: NALTREXONE HYDROCHLORIDE

DOSAGE: TABLET, FILM COATED

ADMINSTRATION: ORAL

NDC: 70518-2718-0

NDC: 70518-2718-1

COLOR: yellow

SHAPE: ROUND

SCORE: Two even pieces

SIZE: 10 mm

IMPRINT: 326

PACKAGING: 30 in 1 BLISTER PACK

PACKAGING: 28 in 1 BLISTER PACK

ACTIVE INGREDIENT(S):

- NALTREXONE HYDROCHLORIDE 50mg in 1

INACTIVE INGREDIENT(S):

- LACTOSE MONOHYDRATE
- CELLULOSE, MICROCRYSTALLINE
- SILICON DIOXIDE
- CROSPOVIDONE
- MAGNESIUM STEARATE
- HYPROMELLOSE 2910 (6 MPA.S)
- TITANIUM DIOXIDE
- POLYETHYLENE GLYCOL 400
- FERRIC OXIDE YELLOW
- POLYSORBATE 80
- FERRIC OXIDE RED